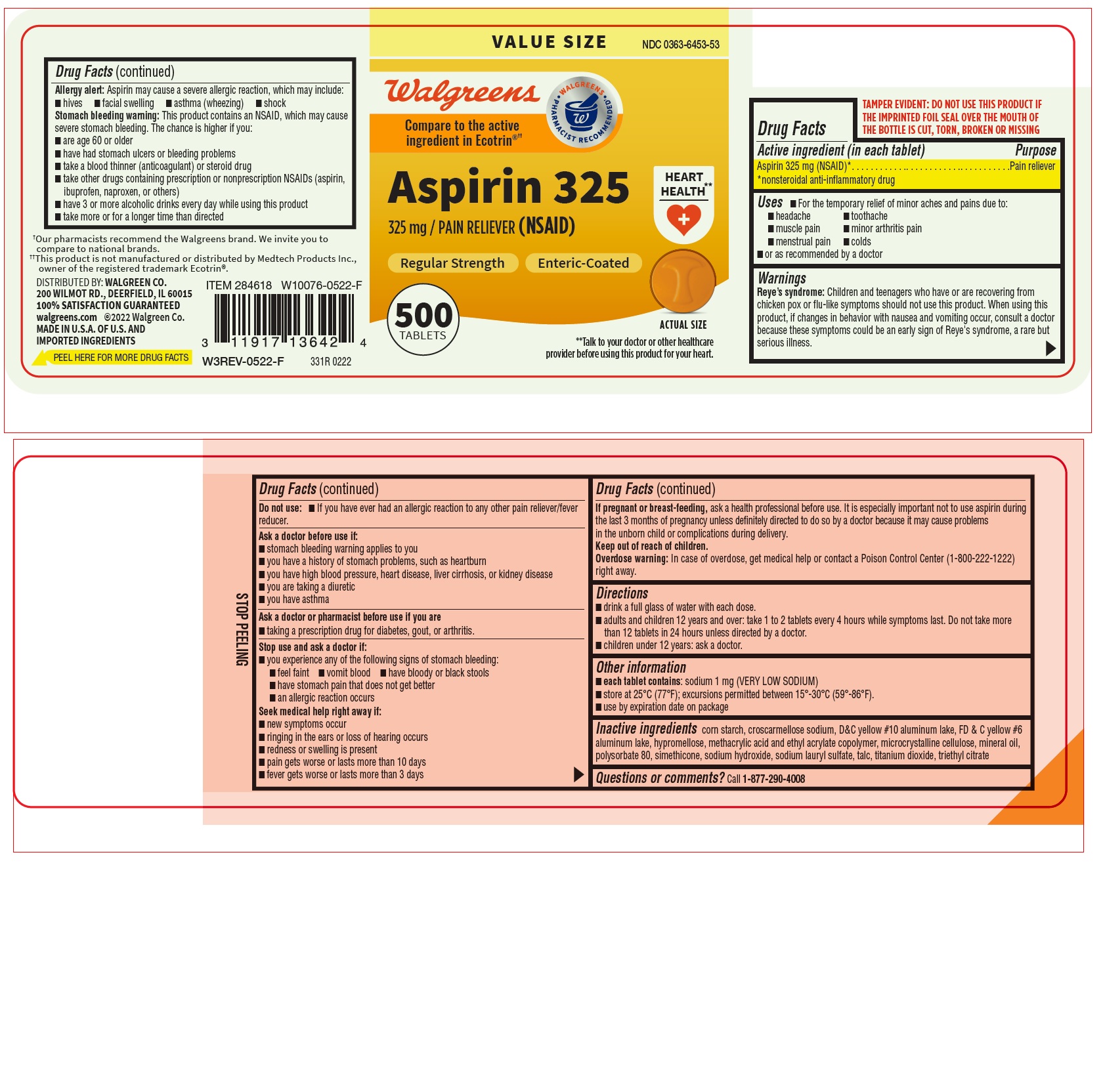 DRUG LABEL: Aspirin 325 mg
NDC: 0363-6453 | Form: TABLET
Manufacturer: WALGREENS
Category: otc | Type: HUMAN OTC DRUG LABEL
Date: 20220708

ACTIVE INGREDIENTS: ASPIRIN 325 mg/1 1
INACTIVE INGREDIENTS: D&C YELLOW NO. 10 ALUMINUM LAKE; HYPROMELLOSE, UNSPECIFIED; MINERAL OIL; POLYSORBATE 80; CROSCARMELLOSE SODIUM; TITANIUM DIOXIDE; MICROCRYSTALLINE CELLULOSE; DIMETHICONE; SODIUM LAURYL SULFATE; METHACRYLIC ACID AND ETHYL ACRYLATE COPOLYMER; FD&C YELLOW NO. 6 ALUMINUM LAKE; SODIUM HYDROXIDE; TRIETHYL CITRATE; STARCH, CORN; TALC

331R Walgreens 0363-6453 Aspirin 325 mg

Active ingredient (in each tablet)
Aspirin 325 mg (NSAID)*
*nonsteroidal anti-inflammatory drug

Purpose
Pain reliever

Uses
• For the temporary relief of minor aches and pains due to:
o headache
o toothache
o muscle pain
o minor arthritis pain
o menstrual pain
o colds
• or as recommended by a doctor

Warnings

Reye's syndrome: Children and teenagers who have or are recovering from chicken pox or flu-like symptoms should not use this product. When using this product, if changes in behavior with nausea and vomiting occur, consult a doctor because these symptoms could be an early sign of Reye's syndrome, a rare but serious illness.

Allergy alert: Aspirin may cause a severe allergic reaction which may include:

- hives
- facial swelling
- asthma (wheezing)
- shock

Stomach bleeding warning: This product contains an NSAID, which may cause severe stomach bleeding. The chance is higher if you:

- are age 60 or older
- have had stomach ulcers or bleeding problems
- take a blood thinner (anticoagulant) or steroid drug
- take other drugs containing prescription or nonprescription NSAIDS (aspirin, ibuprofen, naproxen, or others)
- have 3 or more alcoholic drinks every day while using this product
- take more or for a longer time than directed

Do not use:
• If you have ever had an allergic reaction to any other pain reliever/fever reducer.

Ask a doctor before use if:
• stomach bleeding warning applies to you
• you have a history of stomach problems such as heartburn
• you have high blood pressure, heart disease, liver cirrhosis, or kidney disease
• you are taking a diuretic
• you have asthma

Ask a doctor or pharmacist before use if you are

- taking a prescription drug for diabetes, gout, or arthritis.

Stop use and ask a doctor if:
you experience any of the following signs of stomach bleeding:

- feel faint
- vomit blood
- have bloody or black stools
- have stomach pain that does not get better
- an allergic reaction occurs

Seek medical help right away if:

- new symptoms occur
- ringing in the ears or loss of hearing occurs
- redness or swelling is present
- pain gets worse or lasts more than 10 days
- fever gets worse or lasts more than 3 days

PREGNANCY OR BREAST FEEDING

If pregnant or breast-feeding, ask a health professional before use. It is especially important not to use aspirin during the last 3 months of pregnancy unless definitely directed to do so by a doctor because it may cause problems in the unborn child or complications during delivery.

Keep out of reach of children.
Overdose warning: In case of overdose, get medical help or contact a Poison Control Center (1-800-222-1222) right away.

Directions

- drink a full glass of water with each dose.
- adults and children 12 years and over: take 1 to 2 tablets every 4 hours while symptoms last. Do not take more than 12 tablets in 24 hours unless directed by a doctor.
- children under 12 years: ask a doctor.

Other information
• each tablet contains: sodium 1 mg (VERY LOW SODIUM)
• store at 25°C (77°F); excursions permitted between 15°-30°C (59°-86°F).
• use by expiration date on package

INACTIVE INGREDIENT

Inactive ingredients corn starch, croscarmellose sodium, D&C yellow #10 aluminum lake, FD & C yellow #6 aluminum lake, hypromellose, methacrylic acid and ethyl acrylate copolymer, microcrystalline cellulose, mineral oil, polysorbate 80, simethicone, sodium hydroxide, sodium lauryl sulfate, talc, titanium dioxide, triethyl citrate

Questions or comments? Call 1-877-290-4008